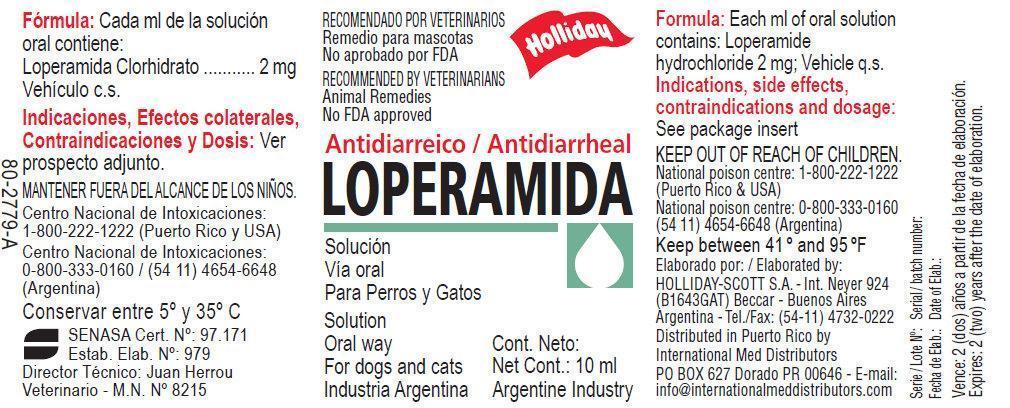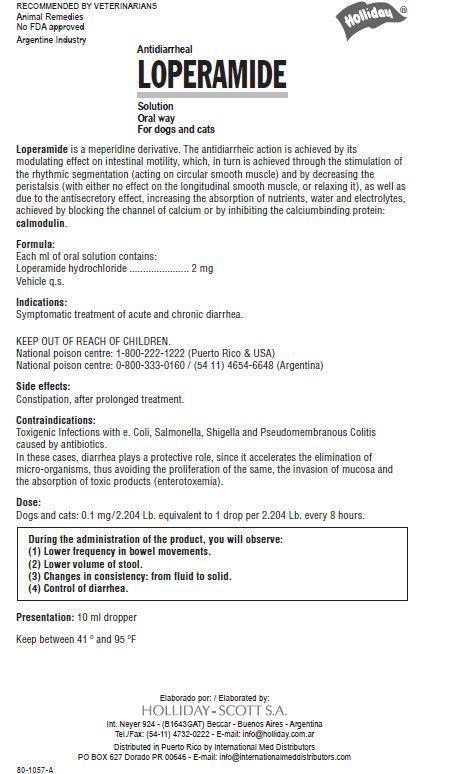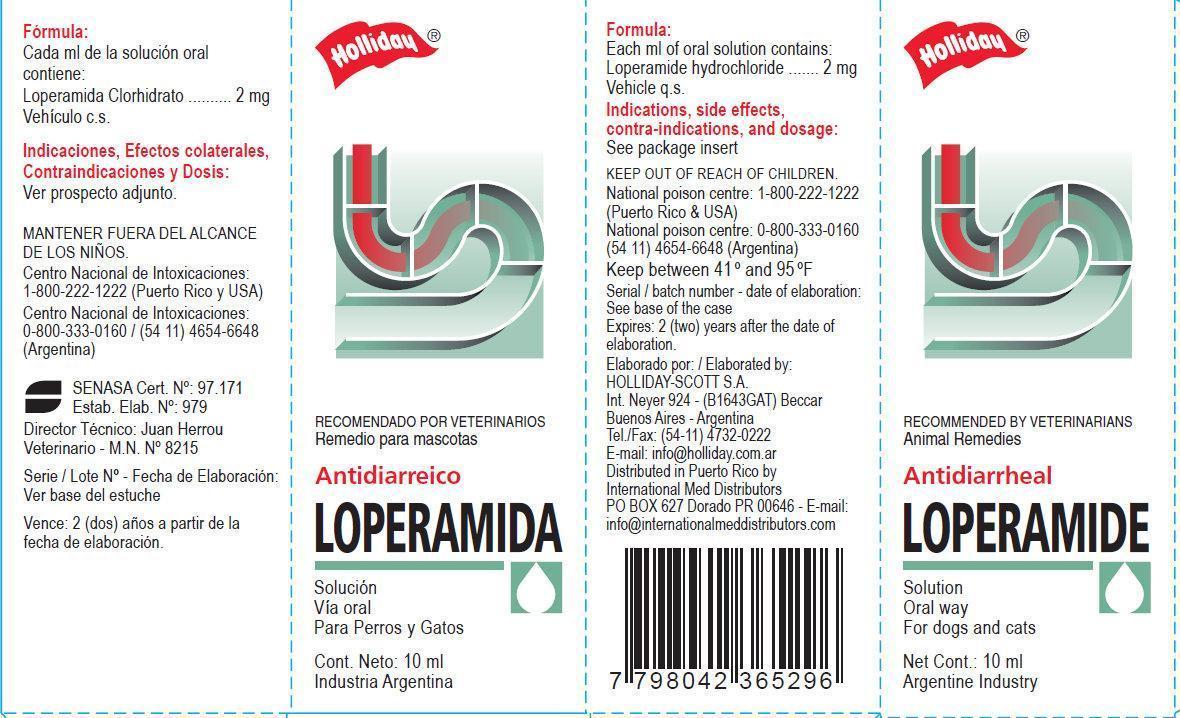 DRUG LABEL: Antidiarrheal LOPERAMIDE
NDC: 58670-000 | Form: SOLUTION
Manufacturer: Holliday-Scott S.A.
Category: animal | Type: OTC ANIMAL DRUG LABEL
Date: 20130731

ACTIVE INGREDIENTS: LOPERAMIDE HYDROCHLORIDE 2 mg/1 mL

Antidiarrheal LOPERAMIDE Solution

Antidiarrheal LOPERAMIDE Solution

Oral Way For dogs and cats Loperamide is meperidine derivative. The antidiarrheic action is achieved by its modulating effect on intestinal motility, which, in turn is achieved through the stimulation of the rhythmic segmentation (acting on circular smooth muscle) and by decreasing the peristalsis (with either no effect on the longitudinal smooth muscle, or relaxing it), as well as due to the antisecretory effect, increasing the absorption of nutrients, water and electrolytes, achieved by blocking the channel of calcium or by inhibiting the calcium binding protein, calmodulin

Formula:

Each ml of oral solution contains:
Loperamide hydrochloride...........2 mg Vehicle q.s.

Indications:

Symptomatic treatment of acute and chronic diarrhea.

KEEP OUT OF REACH OF CHILDREN.

National poison centre: 1-800-222-1222 (Puerto Rico and USA)
National poison centre: 0-800-333-0160 / (54 11) 4654-6648 (Argentina)

Side effects:

Constipation, after prolonged treatment.

Contraindications:

Toxigenic Infections with e. Coli, Salmonella, Shigella and Pseudomembranous Colitis caused by antibiotics. In these cases, diarrhea plays a protective role, since it accelerates the elimination of micro-organisms, thus avoiding the proliferation of the same, the invasion of mucosa and the absorption of toxic products (enterotoxemia).

Dose:

Dogs and cats: 0.1 mg/2.204 Lb. equivalent to 1 drop per 2.204 Lb. every 8 hours.

During the administration of the product, you will observe:
(1) Lower frequency in bowel movements.
(2) Lower volume of stool.
(3) Changes in consistency: from fluid to solid.
(4) Control of diarrhea.

Presentation:

10 ml dropper

Keep between 40 degree and 95 degree F

Elaborado por: / Elaborated by:

HOLLIDAY-SCOTT S.A.
Int. Neyer 924 - (B1643GAT) Beccar
Buenos Aires - Argentina

Tel./Fax: (54-11) 4732-0222
E-mail: info@holliday.com.ar
Distributed in Puerto Rico by
International Med Distributors
PO BOX 627 Dorado PR 00646 - E-mail:
info@internationalmeddistributors.com

7 798042 365296